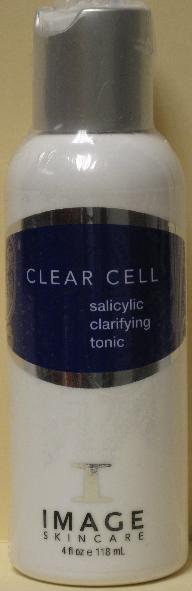 DRUG LABEL: Clear Cell Salicylic Clarifying Tonic
NDC: 62742-4043 | Form: LIQUID
Manufacturer: Allure Labs, Inc.
Category: otc | Type: HUMAN OTC DRUG LABEL
Date: 20100722

ACTIVE INGREDIENTS: SALICYLIC ACID 30 mg/1 mL; GLYCOLIC ACID 50 mg/1 mL

Drug Facts

INDICATIONS AND USAGE SECTION:

A salicylic/glycolic acid skin clarifying removes excess surface oil. A blend of anti-oxidants leaves skin fresh and shine-free.

Paraben Free

DIRECTIONS:

Saturate gauze and gently remove surface oils. Repeat if necessary for additional clarifying and toning.

INDICATIONS:

Acne and acne-prone skin

ACTIVE INGREDIENTS:

Salicylic Acid, Glycolic Acid

INACTIVE INGREDIENTS:

Deionized water (Aqua), Hamamelis virginiana (Witch Hazel) water, Glycerin, Mentha viridis (Spearmint) Oil, Camellia oleifera (Green Tea) leaf extract, Ammonium Hydroxide, Melaleuca alternifolia (Tea tree) leaf oil, Arnica montana flower extract, Chamomile reticutita flower (Chamomile) extract, Aesculus hippocastanum (Horse Chestnut) extract, Melia azadirachta (Neem) extract, Eucalyptus globulus (Eucalyptus) oil.

PACKAGE LABEL

DISTRIBUTOR:

Image International

Palm Beach, FL 33411 USA

www. imageskincare.com

IMAGE OF PRODUCT: